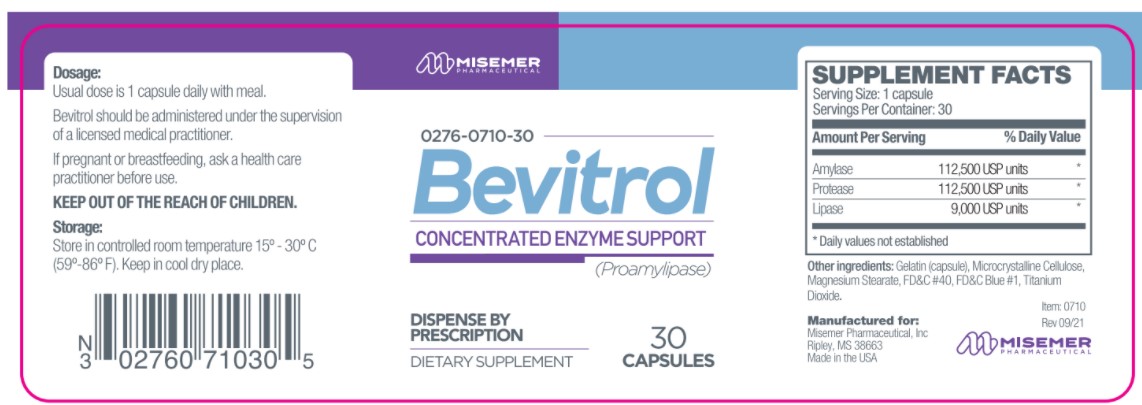 DRUG LABEL: Bevitrol
NDC: 0276-0710 | Form: CAPSULE
Manufacturer: Misemer Pharmaceutical
Category: other | Type: Dietary Supplement
Date: 20211215

ACTIVE INGREDIENTS: PANCRELIPASE AMYLASE 112500 [USP'U]/1 1; PANCRELIPASE PROTEASE 112500 [USP'U]/1 1; PANCRELIPASE LIPASE 9000 [USP'U]/1 1
INACTIVE INGREDIENTS: GELATIN; MICROCRYSTALLINE CELLULOSE; MAGNESIUM STEARATE; FD&C RED NO. 40; FD&C BLUE NO. 1; TITANIUM DIOXIDE

Bevitrol

STATEMENT OF IDENTITY

Bevitrol is an orally administered prescription digestive enzyme dietary supplement formulation for the clinical dietary
management of suboptimal nutritional status in patients where advanced supplementation is required and nutritional
supplementation in physiologically stressful conditions for maintenance of good health is needed.

Bevitrol should be administered under the supervision of a licensed medical practitioner.

DOSAGE AND ADMINISTRATION

Bevitrol is an orally administered prescription digestive enzyme supplement formulation for the clinical dietary
management of suboptimal nutritional status in patients where advanced supplementation is required and nutritional
supplementation in physiologically stressful conditions for maintenance of good health is needed.

Usual adult dose is 1 capsule daily with or without food. Do not exceed 3 capsules per day.

HEALTH CLAIM

Bevitrol is intended for the dietary management of a patient who, because of therapeutic or chronic medical needs, has
limited or impaired capacity to ingest, digest, absorb, or metabolize ordinary foodstuffs or certain nutrients, or who has
other special medically determined nutrient requirements, the dietary management of which cannot be achieved by the
modification of a normal diet alone.

All prescriptions using this product shall be pursuant to state statutes as applicable. This is not an Orange Book product.
This product may be administered only under a physician’s supervision. There are no implied or explicit claims on
therapeutic equivalence.

Manufactured for:
Misemer Pharmaceutical, Inc.
Ripley, MS 38663

Item 0710
Rev. 0921

PRECAUTIONS

Bevitrol should only be used under the direction and supervision of a licensed medical practitioner. Use with caution
in patients that may have a medical condition, are pregnant, lactating, trying to conceive, under the age of 18, or taking
medications.

SAFE HANDLING WARNING

Bevitrol is supplied as red and white capsules dispensed in white HDPE plastic bottles of 30ct.
Item 0276-0710-30
Store at controlled room temperature 15°-30°C (59°F-86°F). Keep in cool dry place. Call your doctor about side effects.
You may report side effects to FDA at 1-800-FDA-1088. KEEP THIS OUT OF THE REACH OF CHILDREN.
Dispense by Prescription

WARNINGS

This product is contraindicated in patients with a known hypersensitivity to any of the ingredients.